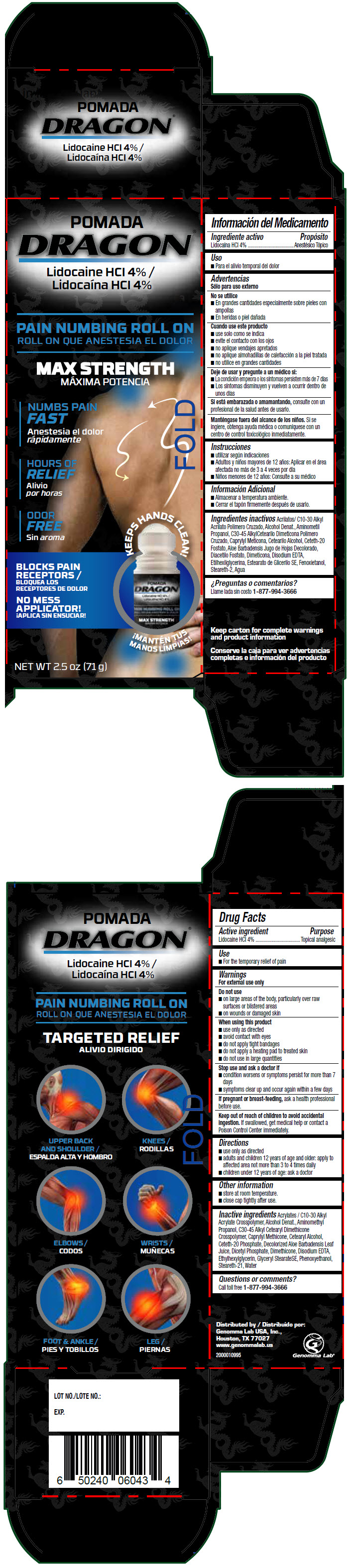 DRUG LABEL: Dragon Pain Numbing Roll-On
NDC: 50066-411 | Form: LIQUID
Manufacturer: Genomma Lab USA
Category: otc | Type: HUMAN OTC DRUG LABEL
Date: 20210726

ACTIVE INGREDIENTS: Lidocaine hydrochloride 40 mg/1 g
INACTIVE INGREDIENTS: Alcohol; Water; AMINOMETHYLPROPANOL; CAPRYLYL TRISILOXANE; ceteth-20 phosphate; Steareth-21

Dragon® Pain Numbing Roll-On

Drug Facts

Active ingredient

Lidocaine HCl 4%

Purpose

Topical analgesic

Use

- For the temporary relief of pain

Warnings

For external use only

Do not use

- on large areas of the body, particularly over raw surfaces or blistered areas
- on wounds or damaged skin

When using this product

- use only as directed
- avoid contact with eyes
- do not apply tight bandages
- do not apply a heating pad to treated skin
- do not use in large quantities

Stop use and ask a doctor if

- condition worsens or symptoms persist for more than 7 days
- symptoms clear up and occur again within a few days

PREGNANCY OR BREAST FEEDING

If pregnant or breast-feeding, ask a health professional before use.

Keep out of reach of children to avoid accidental ingestion. If swallowed, get medical help or contact a Poison Control Center immediately.

Directions

- use only as directed
- adults and children 12 years of age and older: apply to affected area not more than 3 to 4 times daily
- children under 12 years of age: ask a doctor

Other information

- store at room temperature.
- close cap tightly after use.

Inactive ingredients

Acrylates / C10-30 Alkyl Acrylate Crosspolymer, Alcohol Denat., Aminomethyl Propanol, C30-45 Alkyl Cetearyl Dimethicone Crosspolymer, Caprylyl Methicone, Cetearyl Alcohol, Ceteth-20 Phosphate, Decolorized Aloe Barbadensis Leaf Juice, Dicetyl Phosphate, Dimethicone, Disodium EDTA, Ethylhexylglycerin, Glyceryl StearateSE, Phenoxyethanol, Steareth-21, Water

Questions or comments?

Call toll free 1-877-994-3666

Distributed by
Genomma Lab USA, Inc.,
Houston, TX 77027

PRINCIPAL DISPLAY PANEL - 71 g Container Carton

POMADA
DRAGON®

Lidocaine HCl 4%

PAIN NUMBING ROLL ON

MAX STRENGTH

NUMBS PAIN
FAST

HOURS OF
RELIEF

ODOR
FREE

KEEPS HANDS CLEAN!

BLOCKS PAIN
RECEPTORS

NO MESS
APPLICATOR!

NET WT 2.5 oz (71 g)